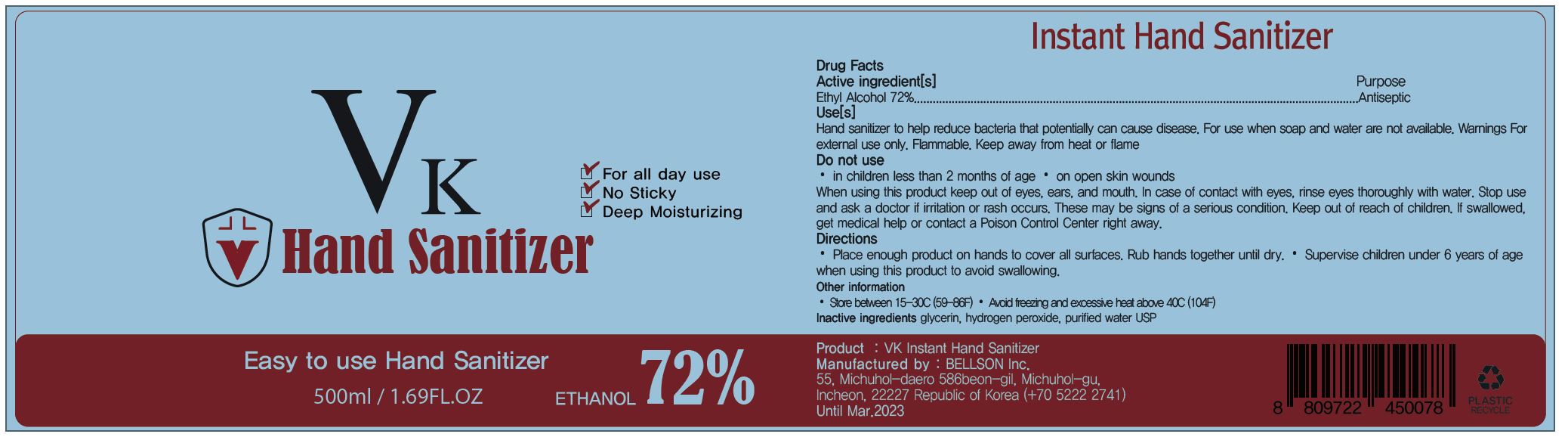 DRUG LABEL: VK HAND SANITIZER
NDC: 75063-0002 | Form: GEL
Manufacturer: BELLESON Inc
Category: otc | Type: HUMAN OTC DRUG LABEL
Date: 20200516

ACTIVE INGREDIENTS: ALCOHOL 72 g/100 mL
INACTIVE INGREDIENTS: HYALURONATE SODIUM; PANTHENOL; BUTYLENE GLYCOL; AMINOMETHYLPROPANOL; CARBOMER 940; ISOPROPYL MYRISTATE; WATER

Drug Facts

ACTIVE INGREDIENT

alcohol

INACTIVE INGREDIENT

Water
Pantenol
Butylene Glycol
Carbomer
Aminomethyl Propanol
Fragrance
Isopropyl Myristate
Sodium Hyaluronate

PURPOSE

to desrease bacteria on hands.

KEEP OUT OF REACH OF THE CHILDREN

INDICATIONS AND USAGE

Place enough product on hands to cover all surfaces. Rub hands together until dry.
Supervise children under 6 years of age when using this product to avoid swallowing

WARNINGS

■ Flammable. Keep away from fire or flame.

■ For external use only.

■ Do not use in eyes.

■ lf swallowed, get medical help promptly.

■ Stop use, ask doctor lf irritation occurs.

■ Keep out of reach of children.

DOSAGE AND ADMINISTRATION

for external use only